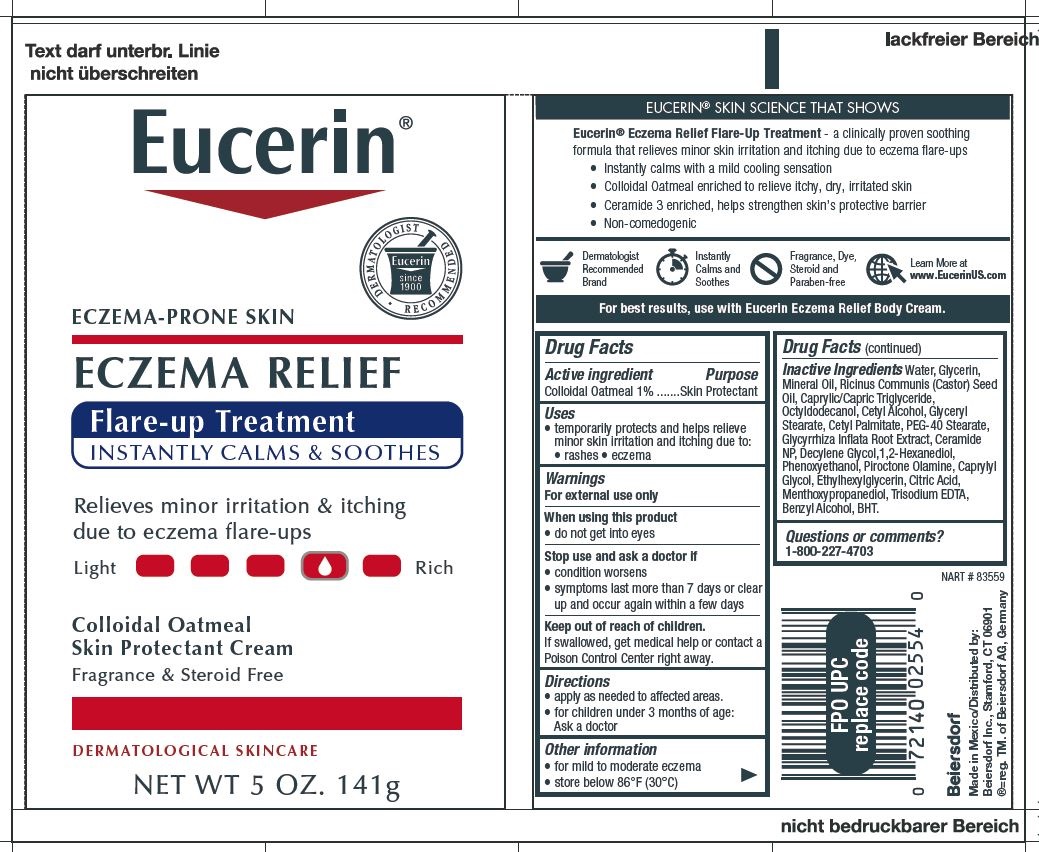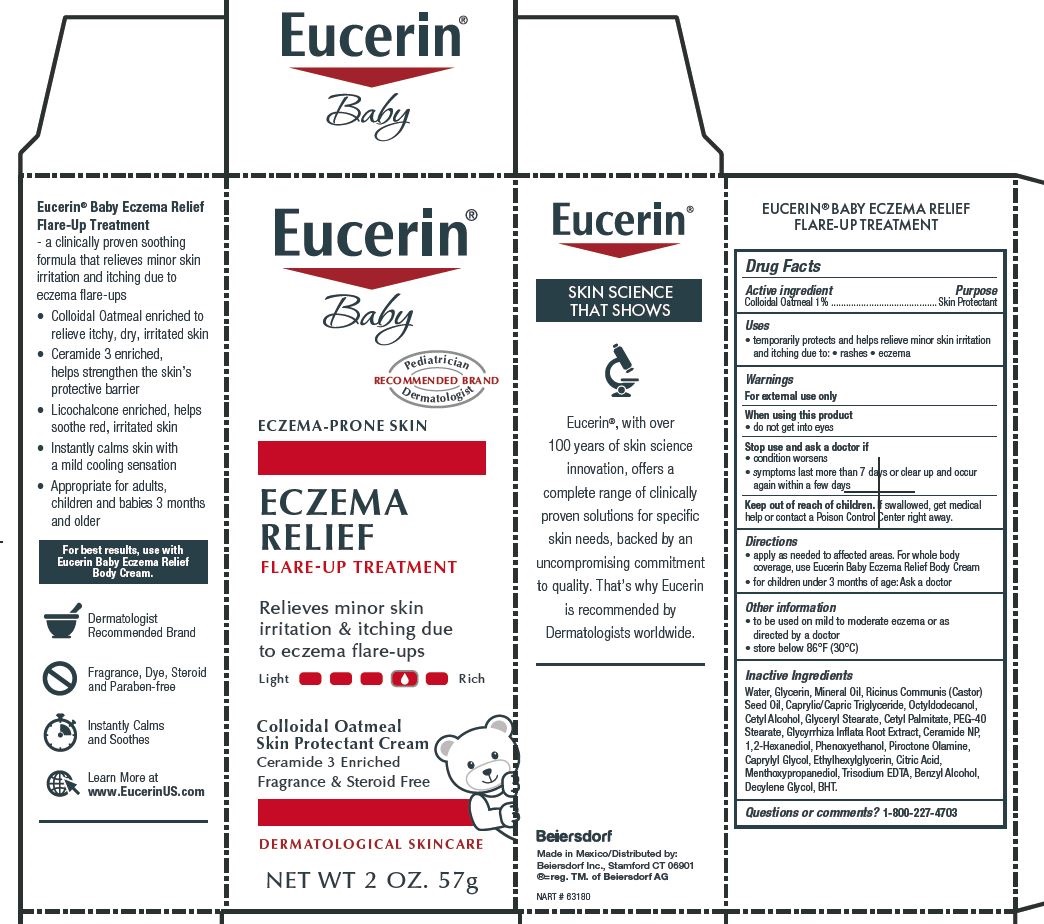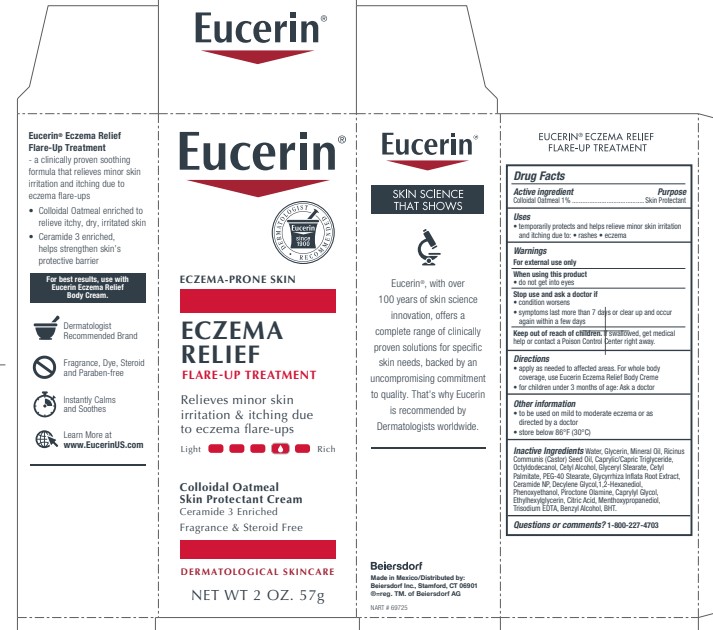 DRUG LABEL: Eucerin Eczema Relief Flare Up Treatment
NDC: 10356-371 | Form: CREAM
Manufacturer: Beiersdorf Inc
Category: otc | Type: HUMAN OTC DRUG LABEL
Date: 20251231

ACTIVE INGREDIENTS: OATMEAL 1 g/100 g
INACTIVE INGREDIENTS: MEDIUM-CHAIN TRIGLYCERIDES; OCTYLDODECANOL; CETYL PALMITATE; PEG-40 STEARATE; GLYCYRRHIZA INFLATA ROOT; CERAMIDE 3; 1,2-HEXANEDIOL; PHENOXYETHANOL; PIROCTONE OLAMINE; CAPRYLYL GLYCOL; ETHYLHEXYLGLYCERIN; BENZYL ALCOHOL; CITRIC ACID MONOHYDRATE; 3-((L-MENTHYL)OXY)PROPANE-1,2-DIOL; EDETATE TRISODIUM; WATER; GLYCERIN; CASTOR OIL; MINERAL OIL; CETYL ALCOHOL; GLYCERYL MONOSTEARATE; DECYLENE GLYCOL; BUTYLATED HYDROXYTOLUENE

Eucerin Eczema Relief Flare Up Treatment

Active ingredients
Colloidal Oatmeal 1%

Warnings
For external use only

When using this product avoid contact with eyes

Stop use and ask a doctor if
condition worsens
symptoms last more than 7 days or clear up and occur again within a few days

Keep out of reach of children. If swallowed, get medical help or
contact a Poison Control Center right away.

Uses
temporarily protects and helps relieve minor skin irritation and itching
due to rashes, eczema

Directions
Apply as needed to affected areas. For whole body coverage, use Eucerin Eczema Relief Body Creme.

Questions or comments?
1-800-227-4703

Inactive Ingredients
Water, Glycerin, Mineral Oil, Ricinus Communis (Castor) Seed Oil,
Caprylic/Capric Triglyceride, Octyldodecanol, Cetyl Alcohol, Glyceryl Stearate,
Cetyl Palmitate, PEG-40 Stearate, Glycyrrhiza Inflata
Root Extract, Ceramide 3, Decylene Glycol, 1,2-Hexanediol, Phenoxyethanol, Piroctone
Olamine, Caprylyl Glycol, Ethylhexylglycerin, Citric Acid, Menthoxypropanediol,
Trisodium EDTA, Benzyl Alcohol, BHT.
.

PURPOSE

Skin protectant

PACKAGE LABEL

Eucerin

Eczema Relief Flare-Up Treatment

Eczema-Prone Skin

Instantly calms and soothes

Colloidal Oatmeal Skin Protectant Cream

Relieves minor skin irritation and
itching due to eczema
flare-ups

Fragrance and Steroid Free

Dermatological skincare

Dermatologist Recommended Brand

Eucerin

Eczema Relief Flare-Up Treatment

Eczema-Prone Skin

Colloidal Oatmeal Skin Protectant Cream

Ceramide 3 Enriched

Relieves minor skin irritation and
itching due to eczema
flare-ups

Fragrance and Steroid Free

Dermatological skincare

Dermatologist Recommended Brand

Eucerin Baby

Eczema Relief Flare-Up Treatment

Eczema-Prone Skin

Colloidal Oatmeal Skin Protectant Cream

Relieves minor skin irritation and

itching due to eczema flare-ups

Fragrance and Steroid Free

Dermatological skincare

Pediatrician and Dermatologist Recommended Brand